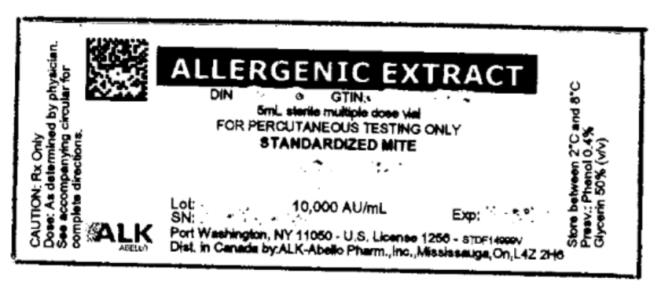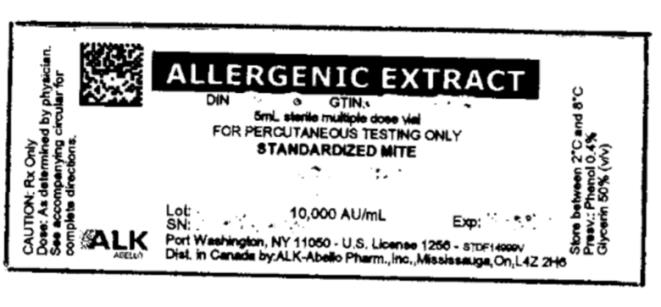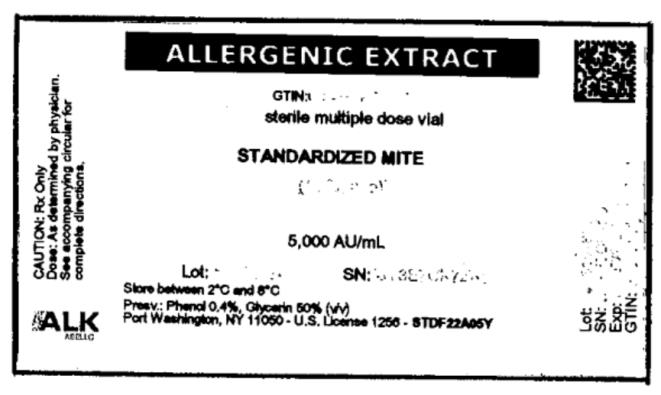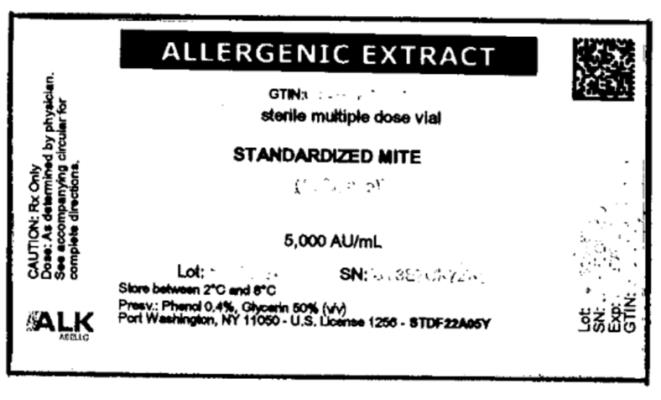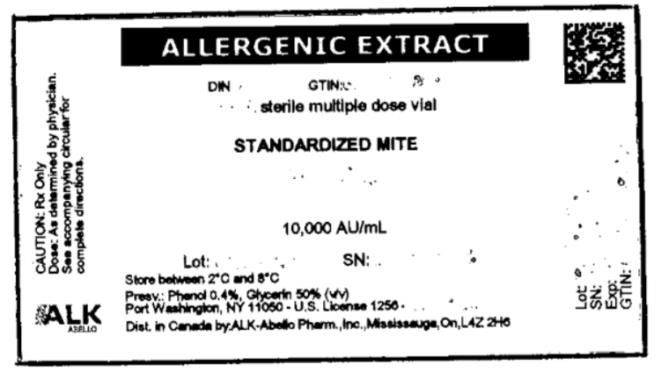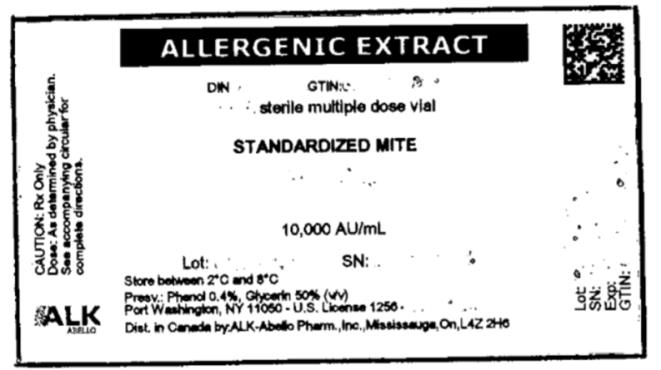 DRUG LABEL: Standardized Mite D. farinae
NDC: 0268-0275 | Form: INJECTION, SOLUTION
Manufacturer: ALK-Abello, Inc.
Category: other | Type: STANDARDIZED ALLERGENIC
Date: 20220811

ACTIVE INGREDIENTS: DERMATOPHAGOIDES FARINAE 10000 [AU]/1 mL
INACTIVE INGREDIENTS: SODIUM CHLORIDE; SODIUM BICARBONATE; GLYCERIN; PHENOL; HYDROCHLORIC ACID; SODIUM HYDROXIDE

Standardized Mite

ALLERGENIC EXTRACT
STANDARDIZED MITE
(Dermatophagoides farinae and Dermatophagoides pteronyssinus)

WARNINGS

Standardized allergenic extract is intended for use by physicians who are experienced in the administration of standardized (AU/mL) allergenic extracts for immunotherapy and the emergency care of anaphylaxis, or for use under the guidance of an allergy specialist. Standardized allergenic extracts are not directly interchangeable with allergenic extracts of the same labeled potency from different manufacturers. The patient must be re-evaluated with the newly selected extract. The initial dose must be based on skin testing as described in the dosage and administration section of this insert. Patients being switched from other types of extracts to standardized allergenic extracts should be started as though they were coming under treatment for the first time. Patients should be instructed to recognize adverse reaction symptoms and cautioned to contact the physician's office if reaction symptoms occur. As with all allergenic extracts, severe systemic reactions may occur. Patients with unstable asthma or steroid dependent asthmatics and patients with underlying cardiovascular disease are at greater risk. In certain individuals, these life-threatening reactions may result in death. Patients should be observed for 20 to 30 minutes following treatment, and emergency measures, as well as personnel trained in their use, should be immediately available in the event of a life-threatening reaction.

This product should not be injected intravenously. Deep subcutaneous routes have proven to be safe. See the warnings, precautions, adverse reactions and over-dosage sections below.

Sensitive patients may experience severe anaphylactic reactions resulting in respiratory obstruction, shock, coma and/or death.

Patients receiving beta-blockers may not be responsive to epinephrine or inhaled bronchodilators. Respiratory obstruction not responding to parenteral or inhaled bronchodilators may require theophylline, oxygen, intubation and the use of life support systems. Parenteral fluid and/or plasma expanders may be utilized for treatment of shock. Adrenocorticosteroids may be administered parenterally or intravenously. Refer to the warnings, precautions and adverse reaction sections below.

Adverse events are to be reported to MedWatch (1-800-FDA-1088), Adverse Event Reporting, Food and Drug Administration, 5600 Fishers Lane, Rockville, MD 20852-9787.

Port Washington, NY 11050

U.S. Government License No. 1256

DESCRIPTION

Allergenic Extract Standardized Mite in the accompanying vial is a sterile solution and contains glycerin 50% v/v and phenol 0.4% (preservative). Inert ingredients include sodium chloride for isotonicity and sodium bicarbonates, as a buffer. The mites (D. farinae and/or D. pteronyssinus),

used as source material for this extract, were cultured by Biopol Laboratories on a medium consisting of yeast and pork. The whole-body mites were separated from the culture medium and the harvested mites contained less than 1% culture medium material.

Several manufacturers submitted to FDA, intradermal skin test data on Biopol Laboratory’s mite medium extract using patients who were puncture test positive (sum of erythema equal to or greater than 40 mm) to either D. farinae or D. pteronyssinus extracts. By intradermal testing, there was 1 positive (sum of erythema equal to or greater than 20 mm) in 44 individuals at an estimated 1% level of medium contamination of mites, and 4 positives in 40 individuals at an estimated 10% contamination. Two of the individuals who were skin test positive also skin tested by the puncture method with an extract of yeast (Saccharomyces sp) and were positive.

In ten mite sensitive patients, ALK-Abelló, Inc. observed no puncture or intradermal reactions to media from the same source at a carryover concentration equivalent to 1% of the mite extract.

For ease in use, and for lot to lot consistency, potency value is expressed in allergy units per milliliter.

This ELISA standardized mite extract was compared to a mite reference preparation supplied by FDA which was labeled 10,000 AU/mL based on skin testing.^1 The relative potency of this mite extract was determined by ELISA inhibition in comparison to the FDA Mite reference and is labeled in AU's (Allergy Units/mL).^2 Dilutions made from this product can be administered intradermally for testing, or subcutaneously for immunotherapy.

CLINICAL PHARMACOLOGY

Diagnostically (for skin testing) the allergen combines with IgE antibodies fixed to mast cells in the skin.^3 This complexing causes an increase in cellular permeability and degranulation of the mast cells releasing chemical mediators. These mediators (such as histamine) are responsible for a local inflammatory response of wheal and erythema typical of a positive skin test reaction and also, the symptoms commonly associated with allergic disease. The more mediator release, the larger the reaction (wheal and erythema).

Treatment consists of the subcutaneous injection of gradually increasing doses of the allergens to which the patient is allergic. It has been demonstrated that this method of treatment induces an increased tolerance to the allergens responsible for the symptoms on subsequent exposure. Although the exact relationships between allergen, skin sensitizing antibody (IgE) and the blocking antibody (IgG) have not been precisely established, clinically confirmed immunological studies have adduced evidence of the efficacy of hyposensitization therapy.

Numerous controlled studies have demonstrated the clinical efficacy of immunotherapy with cat, dust mites and some pollen extracts.^4 Nevertheless, responses are not uniform but variable, and in a few studies, the majority of the patients reported no appreciable improvement.

INDICATIONS AND USAGE

This product is indicated for the diagnosis and treatment of hypersensitivity in patients with symptoms compatible with dust mite allergy.

Hyposensitization (injection) therapy is a treatment for patients exhibiting allergic reactions to seasonal pollens, dust mites, molds, animal danders, and various other inhalants, in situations where the offending allergen cannot be avoided. Mixtures of standardized mite (D. farinae and D. pteronyssinus) should be considered for treatment of patients who are sensitive to both species.

Prior to the initiation of therapy, clinical sensitivity should be established by careful evaluation of the patient's history confirmed by diagnostic skin testing. Hyposensitization should not be prescribed for sensitivities to allergens which can be easily avoided.

CONTRAINDICATIONS

There are no known absolute contraindications to immunotherapy. However, a patient should not be immunized with preparations of allergens to which the patient has not demonstrated symptoms and positive skin tests. In most cases, immunotherapy is not indicated for those allergens that can be eliminated or minimized by environmental control.

Also, there is some evidence, although inconclusive, that routine immunizations may exacerbate autoimmune diseases.^5,6,7 Hyposensitization should be given cautiously to patients with this predisposition. Patients with severe cardiorespiratory symptoms are at additional risk during a systemic reaction. The physician must weigh the risk to benefit in these cases.

Patients on beta-blockers are not candidates for immunotherapy, as they can be non-responsive to beta-agonists that may be required to reverse a systemic reaction. Also, see BOXED WARNING section.

In the presence of active symptoms such as rhinitis, wheezing, dyspnea, etc., the indications of immunotherapy must be weighed carefully against the risk of temporarily aggravating the symptoms by the injection itself.

WARNINGS

See warnings at the beginning of this package insert. Standardized allergenic extracts are not directly interchangeable with allergenic extracts of the same labeled potency from different manufacturers. The patient must be re-evaluated with the newly selected extract.

A reduction in starting dose is recommended in the following circumstances:

1. Changing to a new lot of extract from the same manufacturer
2. Using product from a different manufacturer
3. Using non-standardized extract or any other change in formula
4. Changing to a product bearing a later expiration date
5. When a prolonged lapse in time has occurred since the last injection

Withhold allergenic extracts temporarily or reduce the dose in patients with any one of the following conditions:

- Severe rhinitis or asthma symptoms;

- Infection or flu accompanied by fever;

- Exposure to excessive amounts of clinically relevant allergen prior to therapy.

Allergenic extracts slowly become less potent with age. During the course of treatment, it may be necessary to continue therapy with a vial of extract bearing a later expiration date. The initial dose of the extract bearing the later expiration date should be lowered to a safe non-reaction-eliciting level. When switching one standardized extract with another, at least 75% reduction in dose is suggested.

Patients should always be observed for at least 20 to 30 minutes after any injection. In the event of a marked systemic reaction such as urticaria, angioedema, wheezing, dyspnea, respiratory obstructions, hypotension and coma, application of a tourniquet above the injection site and administration of 0.2 mL to 1.0 mL (0.01 mg/kg) of Epinephrine Injection (1:1000) is recommended. Maximal recommended dose for children between 2 and 12 years of age is 0.5 mL. The tourniquet should not be left in place without loosening for 90 seconds every 15 minutes. Patients under treatment with beta-blockers may be refractory to the usual dose of epinephrine.

Volume expanders and vasopressor agents may be required to reverse hypotension. Inhalation bronchodilators and parenteral aminophylline may be required to reverse bronchospasm. In cases of respiratory obstruction, oxygen and intubation may be necessary. Life-threatening reactions unresponsive to the above may require cardiopulmonary resuscitation. DO NOT GIVE INTRAVENOUSLY.

Mite Extracts (D. farinae and/or D. pteronyssinus) contain small (<1%) amounts of residual media components (pork and yeast). The physician should proceed with caution when using mite extract in mite sensitive individuals that also demonstrate sensitivity to these media components and only if clearly warranted.

In the presence of active symptoms such as rhinitis, wheezing, dyspnea, etc., the indications of immunotherapy must be weighed carefully against the risk of temporarily aggravating the symptoms by the injection itself. If the protective action of allergenic extract injections is considered essential for the patient's welfare, appropriate symptomatic therapy with antihistaminic, adrenergic or other drugs might be needed either prior to or in conjunction with allergenic extract injections.

PRECAUTIONS

INFORMATION TO PATIENTS:

Patients should be instructed to describe any active allergic symptoms such as rhinitis, wheezing, dyspnea, etc., prior to injection including any late reactions from previous administration. Patients should remain in doctor's office for 20-30 minutes following injections and be instructed to report any local or systemic symptoms before leaving. Also, see ADVERSE REACTIONS and WARNINGS Sections.

If the protective action of allergenic extract injections is considered essential for the patient's welfare, appropriate symptomatic therapy with antihistaminic, adrenergic or other drugs might be needed either prior to or in conjunction with the allergenic extract injections.

GENERAL

1. Store allergenic extracts between 2o - 8oC at all times, even during use.
2. Use sterile precautions. Using a sterile tuberculin syringe, injections are given subcutaneously. A separate syringe must be used for each patient to prevent transmission of hepatitis and other infectious disease.
3. Care must be taken to avoid injecting into a blood vessel. Pull gently on syringe plunger to determine if a blood vessel has been entered (See Warnings).
4. Extracts in 50% glycerin can cause discomfort at the site of the injection during the injection.
5. Standardized concentrates of allergenic extracts must be diluted prior to initiation of immunotherapy.
6. Dilute allergenic extracts may be more potent when diluted with Albumin saline than those which do not contain stabilizers such as albumin.

PREGNANCY - CATEGORY C:

Animal reproduction studies have not been conducted with allergenic extracts. It is also not known whether allergenic extracts can cause fetal harm when administered to a pregnant woman or can affect reproduction capacity.

Controlled studies of hyposensitization with moderate to high doses of allergenic extracts during conception and all trimesters of pregnancy have failed to demonstrate any risk to the fetus or to the mother. However, on the basis of histamine's known ability to contract the uterine muscle, the release of significant amounts of histamine from allergen exposure of hyposensitization overdose should be avoided on theoretical grounds. Therefore, allergenic extracts should be used cautiously in a pregnant woman, and only if the benefit outweighs the risk.

PEDIATRIC USE:

Children can receive the same dose as adults, however, to minimize the discomfort associated with dose volume it may be advisable to reduce the volume of the dose by half and administer the injection at two different sites.

GERIATRIC USE:

Studies in geriatric patients have not been conducted. Physicians should consider risk to benefit of immunotherapy in this patient population.

NURSING MOTHERS:

It is not known if allergens administered subcutaneously appear in human milk. Because many drugs are excreted in human milk, caution should be exercised when allergenic extracts are administered to a nursing woman.

CARCINOGENESIS, MUTAGENESIS, IMPAIRMENT OF FERTILITY:

Long term studies in animals have not been performed.

DRUG INTERACTIONS:

Drugs can interfere with the performance of skin tests.^8

Antihistamines: Response to mediator (histamine) released by allergens is suppressed by antihistamines. The length of suppression varies and is dependent on individual patient, type of antihistamine and length of time the patient has been on antihistamines. The duration of this suppression may be as little as 24 hours to several days.

Tricyclic Antidepressants: These exert a potent and sustained decrease of skin reactivity to histamine which may last for a few weeks.

Beta2 Agonists: Oral terbutaline and parenteral ephedrine, in general, have been shown to decrease allergen induced wheal.

Dopamine: Intravenous infusion of dopamine may inhibit skin test responses.

Beta Blocking Agents: Propranolol can significantly increase skin test reactivity (See WARNINGS).

Other Drugs: Short acting steroids, inhaled beta2 agonists, theophylline and cromolyn do not seem to affect skin test response.

ADVERSE REACTIONS

Local: Reactions at the site of injection may be immediate or delayed. Immediate wheal and erythema reactions are ordinarily of little consequence, but if very large, may be the first manifestation of systemic reaction. If large local reactions occur, the patient should be observed for systemic symptoms for which treatment is outlined below. However, systemic reactions may occur in the absence of large local reactions.

Delayed reactions start several hours after injection with local edema, erythema, itching or pain. They are usually at their peak at 24 hours and usually require no treatment. Antihistamine drugs may be administered orally.

The next therapeutic dose should be reduced to the dose which did not elicit a reaction, and subsequent doses increased more slowly, i.e., use of intermediate dilutions.

Systemic: Reports from regulatory authorities in Sweden to the FDA, indicated that several deaths have been associated with the use of mite extracts. The FDA was subsequently informed that these deaths may have been related to use by physicians untrained in the administration of potent extracts rather than a product defect. It should be noted that anaphylaxis and deaths following the injection of mite and other extracts have also been reported by The British Committee on Safety in Medicine.^9 Fatalities from immunotherapy in the United States since 1945 have been extensively reviewed by Lockey, R F, et al^10, Reid M J et al.^11 and more recently by Bernstein, D. I. et al^23 . With careful attention to dosage and administration, such reactions occur infrequently, but it must be remembered that allergenic extracts are highly potent to sensitive individuals and OVERDOSE could result in anaphylactic symptoms. Therefore, it is imperative that physicians administering allergenic extracts understand and be prepared for the treatment of severe reactions.

Systemic reactions are characterized by one or more of the following symptoms: Sneezing, mild to severe general urticaria, itching other than at the injection site, extensive or generalized edema, wheezing, asthma, dyspnea, cyanosis, hypotension, syncope and upper airway obstruction. Symptoms may progress to shock and death. Patients should always be observed for 20 to 30 minutes after any injection. Volume expanders and vasopressor agents may be required to reverse hypotension. Inhalational bronchodilators and parenteral aminophylline may be required to reverse bronchospasm. Severe airway obstruction, unresponsive to bronchodilator, may require tracheal intubation and use of oxygen. In the event of a marked systemic reaction, application of a tourniquet above the injection site and the administration 0.2 mL to 1.0 mL of Epinephrine Injection (1:1000) is recommended. Maximal recommended dose for children under 2 years of age is 0.3 mL. Maximal recommended dose for children between 2 and 12 years of age is 0.5 mL. The tourniquet should not be left in place without loosening for 90 seconds every 15 minutes.

The next therapeutic injection of extract should be reduced to the dose which did not elicit a reaction, and subsequent doses increased more slowly, i.e., use of intermediate dilutions.

OVERDOSE

Signs and symptoms of overdose are typically local and systemic reactions. For a description and management of overdose reactions, refer to "Adverse Reactions" section above.

DOSAGE AND ADMINISTRATION

Parenteral drug products should be inspected visually for particulate matter and discoloration prior to administration whenever solution and container permit.

When diluting bulk extracts, use of either Sterile Diluent for Allergenic Extracts or Sterile Diluent for Allergenic Extracts Normal Saline with HSA is recommended. Dilutions should be made with sterile disposable syringes using aseptic technique. Commonly 10 fold dilutions are used to achieve a desired concentration for intradermal testing or initiation and continuation of immunotherapy. For example, transferring 0.5 mL of a 10,000 AU/mL extract into 4.5 mL of diluent will yield 5 mL of extract @ 1,000 AU/mL. Prepare as many additional serial dilutions as necessary to reach the appropriate concentration.

Care should be exercised to avoid cross contamination of allergens if mixing with other allergenic extracts. The use of separate syringes for each allergen and diluent when compounding patient mixes is recommended.

Diagnosis - In diagnosing the sensitive individual, the symptom history must be associated with exposure to the allergen. Skin testing is used in conjunction with a definitive history for diagnosing individual sensitivities.

An excellent method of recording results is to cover the skin reaction with transparent tape, outline the erythema first then the wheal with an indelible pen, then remove the tape and transfer it to the patient's permanent record. For preferred results, it is recommended that the actual measurement of the extent of both responses be recorded. This can be accomplished by measuring the longest erythema diameter, then selecting the mid - point of that line and measuring at a 90○ angle to that line to determine the orthogonal diameter. The sum of these two measurements is the sum of erythema (ƩE); the sum of wheal diameters is determined in a similar manner.

Patient's response is graded on the basis of the size of erythema and/or wheal.

Percutaneous (prick/scratch/puncture) test:

Prick, scratch, or puncture skin tests should be performed initially using an extract specially made for this purpose. The usual dose is one drop.

In a skin test study of 10 patients who were determined to be allergic to mite (D. farinae), the mean puncture test (using a bifurcated needle) to a solution containing 10,000 AU/mL had a sum of erythema of 73 mm (range 43 - 138 mm) and a sum of wheal of 17 mm (range 7 - 31 mm).

In another skin test study of 11 patients who were determined to be allergic to mite (D. pteronyssinus), the mean puncture test (using a bifurcated needle) to a solution containing 10,000 AU/mL had a sum of erythema of 84 mm (range 56 - 112 mm) and a sum of wheal of 20 mm (range 7 - 33 mm).

What follows are general guidelines for percutaneous testing. Different devices and/or techniques influence the size of the reaction, therefore it is important to refer to the device manufacturer's or distributor's instructions when grading reactions.

0 No wheal. Erythema absent or very slight (not more than 1 mm in diameter).

+ Wheal absent or very slight erythema present (not more than 3 mm diameter).

++ Wheal not more than 3 mm diameter, or erythema not more than 5 mm diameter.

+++ Wheal between 3 mm and 5 mm in diameter with erythema. Possible pseudopodia and itching.

++++ Any larger reaction with itching and possible pain.

Intradermal test:

On the forearm or upper outer aspect of the arm, using a 26 - 27 gauge, short bevel needle, inject intradermally .05 mL of the intradermal test solution. Skin whealing responses should be observed 10 - 20 minutes after administering the test.

In a skin test study of the 10 mite puncture reactive patients (D. farinae) described above, the mean intradermal dose for ƩE = 50 mm was 0.01 AU/mL (range = <0.0003 to 0.4 AU/mL).

In the skin test study of the 11 mite puncture reactive patients (D. pteronyssinus) described above, the mean intradermal dose for ƩE = 50 mm was 0.006 AU/mL (range = <0.0007 to 0.05 AU/mL).

Intradermal testing should start with a dilute solution, usually in the range of 1 AU or less.

Glycerinated extracts diluted for intradermal testing may be diluted at least 25 fold to less than 2% glycerin (by volume) as glycerin above this level can cause false positive intradermal skin tests.

A negative skin test is one where the sum of erythema was 0 or equal to the sum of the wheal. As a negative control, the diluent should be tested and included in the interpretation of the skin reactions.

0 No increase in size of bleb since injection. No erythema.

+ An increase in size of bleb and a wheal not more than 5 mm diameter with associated erythema.

++ Wheal between 5 mm and 8 mm in diameter with erythema.

+++ Wheal between 8 mm and 12 mm in diameter with erythema and possible pseudopodia, itching or pain.

++++ Any larger reaction with itching and pain and possible diffuse blush of the skin surrounding the reaction area.

Immunotherapy - Starting dose for immunotherapy is related directly to a patient's sensitivity as determined by carefully executed skin testing. Degree of sensitivity can be established by determination of D50 (the intradermal dose, base three, that produces a ƩE = 50 mm).^1

A general rule is to begin at 1/10 of the dose that produces sum of erythema of 50 mm (approximately a 2+ positive skin test reaction). For example, if a patient exhibits a 2+ intradermal reaction to

1 AU/mL, the first dose should be no higher than 0.05 mL of 0.1 AU/mL. Dosage may be increased by 0.05 mL each time until 0.5 mL is reached, at which time the next 10-fold more concentrated dilution can be used, beginning with 0.05 mL, if no untoward reaction is observed. (See beginning of DOSAGE AND ADMINISTRATION section for instructions in preparing dilutions of concentrates.)

If a tolerated dose of allergenic extract has been established, the initial dose from the new extract should be reduced by 75% of the previously well tolerated dose (see also Precautions).

Interval between doses in the early stages of immunotherapy is no more than once to twice a week, and may gradually be increased to once every two weeks. Generally, maintenance injections may be given as infrequently as once every two weeks to once a month. The progress of patients on immunotherapy should be closely monitored. If improvement is realized a usual course of treatment may be from 3 to 5 years. If progress is unsatisfactory for a year or more, discontinuation of immunotherapy should be considered.

Injections are given subcutaneously preferably in the arm. It is advantageous to give injections in alternate arms and routinely in the same area. In some patients, a local tolerance to the allergen may develop thus preventing a possible severe local reaction.

After inserting the needle, but before injecting the dose, pull plunger of the syringe slightly, if blood returns in the syringe, discard the syringe and contents and repeat injection at another site.

Bulk concentrated extracts must be diluted for initial therapy and intradermal skin testing. For recommended diluent, refer to the beginning of the DOSAGE AND ADMINISTRATION section.

Use standard aseptic precautions when making dilutions. The first dose of the new extract should be reduced at least 50% - 75% of the amount of the dosage from the previous extract.

Stability studies for diluted and undiluted forms of this product are not complete. Indications are the undiluted product will retain its potency under recommended storage conditions at least until the expiration date on the vial label is reached. It is recommended that minimal amounts of the concentrate be diluted so that the diluted product is used up within a relatively short period of time, i.e., preferably not more than four weeks.

HOW SUPPLIED

For percutaneous testing, 5 mL vial, 10,000 AU/mL in glycerin 50% (V/V).

For immunotherapy, 10 mL, 30 mL and 50 mL vials of bulk concentrate, 10,000 AU/mL in glycerin 50% (V/V).

STORAGE:

To maintain stability of allergenic extracts, proper storage conditions are essential. Bulk concentrates and diluted extracts are to be stored at 2o to 8o C even during use. Bulk or diluted extracts are not to be frozen. Do not use after the expiration date shown on the vial label.

REFERENCES

^1Turkeltaub, P. C. et al. Office of Biologics Research and Review skin test method for evaluation of subject sensitivity to standardized allergenic extracts and for assignment of allergy units to reference preparations using the ID50EAL method. FDA OBRR Methods of the Allergenic Products Branch. 1986.

^2 Anon. ELISA Competition Assay: Quantitative determination of relative potency of Allergenic Extracts. FDA CBER Methods of the Allergenics Products Testing Laboratory. 1993.

^3 Norman, P. S. The clinical significance of IgE. Hosp. Prac. 1975; 10:41-49.

^4 VanMetre, T. E. and Adkinson, N. F. Immunotherapy for aeroallergen disease. In: Middleton et al. Allergy Principles and Practice 3rd Ed. St. Louis: CV Mosby, 1988:1327.

^5 Umetsu, D. T. et al. Serum sickness triggered by anaphylaxis: a complication of immunotherapy. J. Allergy Clin. Immunol. 1985; 76:713.

^6 Phannphak, P. and Kohler, P. F. Onset of polyarteritis nodosa during allergic hyposensitization treatment. Am. J. Med. 1980; 68:479.

^7 Kohler, P. F. Immune complexes and allergic disease. In: Middleton et al. Allergy Principles and Practice 3rd Ed. St. Louis: CV Mosby, 1988:167.

^8 Bousquet, J.: In vivo methods for the study of allergy: skin test, techniques, and interpretation. In: Middleton et al: Allergy Principles and Practice 3rd Ed. St. Louis: CV Mosby, 1988:167.

^9 Committee on the Safety of Medicines. CSM update: desensitizing vaccines. Brit. Med. J. 1986; 293:948.

^10 Lockey, R. F. et al. Fatalities from immunotherapy(IT) and skin testing (ST). J. Allergy Clin. Immunol. 1987; 79:660.

^11 Reid M J et al. Survey of fatalities from skin testing and immunotherapy 1985-1989. J. Allergy Clin. Immunol. 1993; 92:6.

^12Bernstein DI, Wanner M, Borish L, Liss GM: Immunotherapy Committee, American Academy of Allergy, Asthma and Immunology. Twelve-year survey of fatal reactions to allergen injections and skin testing: 1990-2001. J Allergy Clin Immunol. 204 Jun;113(6):1129-36.

Distributed in Canada by:

Alk-Abelló Pharmaceuticals, Inc.

#35-151 Brunel Road

Mississauga, Ontario Canada, L4Z 2H6

Revision: July 2016

©ALK-Abelló, Inc. 188L

PRINCIPAL DISPLAY PANEL

ALLERGENIC EXTRACT
FOR PERCUTANEOUS TESTING ONLY
STANDARDIZED MITE
10,000 AU/mL

PRINCIPAL DISPLAY PANEL

ALLERGENIC EXTRACT
STANDARDIZED MITE
5,000 AU/mL

PRINCIPAL DISPLAY PANEL

ALLERGENIC EXTRACT
sterile multiple dose vial
STANDARDIZED MITE
10,000 AU/mL